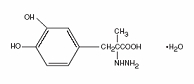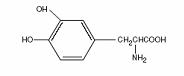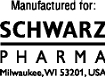 DRUG LABEL: Unknown
Manufacturer: Schwarz Pharma
Category: prescription | Type: Human prescription drug label
Date: 20071105

PARCOPA®
(carbidopa-levodopa orally disintegrating tablets)
RX ONLY

Description

PARCOPA® (carbidopa-levodopa orally disintegrating tablets) is a combination of carbidopa and levodopa for the treatment of Parkinson’s disease and syndrome. PARCOPA® is an orally administered formulation of carbidopa-levodopa which rapidly disintegrates on the tongue and does not require water to aid dissolution or swallowing.

Carbidopa, an inhibitor of aromatic amino acid decarboxylation, is a white, crystalline compound, slightly soluble in water, with a molecular weight of 244.24. It is designated chemically as (–)-L-α-hydrazino-α-methyl-ß-(3,4-dihydroxybenzene) propanoic acid monohydrate. Its empirical formula is C10H14N2O4•H2O, and its structural formula is:

Tablet content is expressed in terms of anhydrous carbidopa which has a molecular weight of 226.23.

Levodopa, an aromatic amino acid, is a white, crystalline compound, slightly soluble in water, with a molecular weight of 197.2. It is designated chemically as (–)-L-α-amino-ß-(3,4-dihydroxybenzene) propanoic acid. Its empirical formula is C9H11NO4, and its structural formula is:

PARCOPA® is supplied as tablets in three strengths:

PARCOPA® 25/100, containing 25 mg of carbidopa and 100 mg of levodopa.

PARCOPA® 10/100, containing 10 mg of carbidopa and 100 mg of levodopa.

PARCOPA® 25/250, containing 25 mg of carbidopa and 250 mg of levodopa.

Inactive ingredients are aspartame, citric acid, crospovidone, magnesium stearate, mannitol, microcrystalline cellulose, natural and artificial mint flavor and sodium bicarbonate. PARCOPA® 10/100 and 25/250 also contain FD&C blue #2 HT aluminum lake. PARCOPA® 25/100 also contains yellow 10 iron oxide.

Clinical Pharmacology

Parkinson’s disease is a progressive, neurodegenerative disorder of the extrapyramidal nervous system affecting the mobility and control of the skeletal muscular system. Its characteristic features include resting tremor, rigidity, and bradykinetic movements. Symptomatic treatments, such as levodopa therapies, may permit the patient better mobility.

Mechanism of Action

Current evidence indicates that symptoms of Parkinson’s disease are related to depletion of dopamine in the corpus striatum. Administration of dopamine is ineffective in the treatment of Parkinson’s disease apparently because it does not cross the blood-brain barrier. However, levodopa, the metabolic precursor of dopamine, does cross the blood-brain barrier, and presumably is converted to dopamine in the brain. This is thought to be the mechanism whereby levodopa relieves symptoms of Parkinson’s disease.

Pharmacodynamics

When levodopa is administered orally it is rapidly decarboxylated to dopamine in extracerebral tissues so that only a small portion of a given dose is transported unchanged to the central nervous system. For this reason, large doses of levodopa are required for adequate therapeutic effect and these may often be accompanied by nausea and other adverse reactions, some of which are attributable to dopamine formed in extracerebral tissues.

Since levodopa competes with certain amino acids for transport across the gut wall, the absorption of levodopa may be impaired in some patients on a high protein diet.

Carbidopa inhibits decarboxylation of peripheral levodopa. It does not cross the blood-brain barrier and does not affect the metabolism of levodopa within the central nervous system.

The incidence of levodopa-induced nausea and vomiting is less with carbidopa-levodopa than with levodopa. In many patients, this reduction in nausea and vomiting will permit more rapid dosage titration.

Since its decarboxylase inhibiting activity is limited to extracerebral tissues, administration of carbidopa with levodopa makes more levodopa available for transport to the brain.

Pharmacokinetics

Carbidopa reduces the amount of levodopa required to produce a given response by about
75 percent and, when administered with levodopa, increases both plasma levels and the plasma half-life of levodopa, and decreases plasma and urinary dopamine and homovanillic acid.

The plasma half-life of levodopa is about 50 minutes, without carbidopa. When carbidopa and levodopa are administered together, the half-life of levodopa is increased to about 1.5 hours. At steady state, the bioavailability of carbidopa from carbidopa-levodopa tablets is approximately 99% relative to the concomitant administration of carbidopa and levodopa.

In clinical pharmacologic studies, simultaneous administration of carbidopa and levodopa produced greater urinary excretion of levodopa in proportion to the excretion of dopamine than administration of the two drugs at separate times.

Pyridoxine hydrochloride (vitamin B6), in oral doses of 10 mg to 25 mg, may reverse the effects of levodopa by increasing the rate of aromatic amino acid decarboxylation. Carbidopa inhibits this action of pyridoxine; therefore, PARCOPA® can be given to patients receiving supplemental pyridoxine (vitamin B6).

Indications and Usage

PARCOPA® is indicated in the treatment of the symptoms of idiopathic Parkinson’s disease (paralysis agitans), postencephalitic parkinsonism, and symptomatic parkinsonism which may follow injury to the nervous system by carbon monoxide intoxication and/or manganese intoxication. PARCOPA® is indicated in these conditions to permit the administration of lower doses of levodopa with reduced nausea and vomiting, with more rapid dosage titration, with a somewhat smoother response, and with supplemental pyridoxine (vitamin B6).

In some patients, a somewhat smoother antiparkinsonian effect results from therapy with carbidopa-levodopa than with levodopa. However, patients with markedly irregular (“on-off”) responses to levodopa have not been shown to benefit from carbidopa-levodopa therapy.

Although the administration of carbidopa permits control of parkinsonism and Parkinson’s disease with much lower doses of levodopa, there is no conclusive evidence at present that this is beneficial other than in reducing nausea and vomiting, permitting more rapid titration, and providing a somewhat smoother response to levodopa.

Certain patients who responded poorly to levodopa have improved when carbidopa-levodopa was substituted. This is most likely due to decreased peripheral decarboxylation of levodopa which results from administration of carbidopa rather than to a primary effect of carbidopa on the nervous system. Carbidopa has not been shown to enhance the intrinsic efficacy of levodopa in parkinsonian syndromes.

In considering whether to give PARCOPA® to patients already on levodopa who have nausea and/or vomiting, the practitioner should be aware that, while many patients may be expected to improve, some do not. Since one cannot predict which patients are likely to improve, this can only be determined by a trial of therapy. It should be further noted that in controlled trials comparing carbidopa-levodopa with levodopa, about half of the patients with nausea and/or vomiting on levodopa improved spontaneously despite being retained on the same dose of levodopa during the controlled portion of the trial.

Contraindications

Nonselective monoamine oxidase (MAO) inhibitors are contraindicated for use with PARCOPA®. These inhibitors must be discontinued at least two weeks prior to initiating therapy with PARCOPA®. PARCOPA® may be administered concomitantly with the manufacturer’s recommended dose of an MAO inhibitor with selectivity for MAO type B
(e.g., selegiline HCl) (See Precautions, Drug interactions).

PARCOPA® is contraindicated in patients with known hypersensitivity to any component of this drug, and in patients with narrow-angle glaucoma.

Because levodopa may activate a malignant melanoma, PARCOPA® should not be used in patients with suspicious, undiagnosed skin lesions or a history of melanoma.

Warnings

When PARCOPA® (carbidopa-levodopa orally disintegrating tablets) is to be given to patients who are being treated with levodopa, levodopa must be discontinued at least twelve hours before therapy with PARCOPA® (carbidopa-levodopa orally disintegrating tablets) is started. In order to reduce adverse reactions, it is necessary to individualize therapy. See Dosage and Administration section before initiating therapy.

The addition of carbidopa with levodopa in the form of PARCOPA® reduces the peripheral effects (nausea, vomiting) due to decarboxylation of levodopa; however, carbidopa does not decrease the adverse reactions due to the central effects of levodopa. Because carbidopa permits more levodopa to reach the brain and more dopamine to be formed, certain adverse CNS effects, e.g., dyskinesias (involuntary movements), may occur at lower dosages and sooner with PARCOPA® than with levodopa alone.

Levodopa alone, as well as PARCOPA®, is associated with dyskinesias. The occurrence of dyskinesias may require dosage reduction.

As with levodopa, PARCOPA® may cause mental disturbances. These reactions are thought to be due to increased brain dopamine following administration of levodopa. All patients should be observed carefully for the development of depression with concomitant suicidal tendencies. Patients with past or current psychoses should be treated with caution.

PARCOPA® should be administered cautiously to patients with severe cardiovascular or pulmonary disease, bronchial asthma, renal, hepatic or endocrine disease.

As with levodopa, care should be exercised in administering PARCOPA® to patients with a history of myocardial infarction who have residual atrial, nodal, or ventricular arrhythmias. In such patients, cardiac function should be monitored with particular care during the period of initial dosage adjustment, in a facility with provisions for intensive cardiac care.

As with levodopa, treatment with PARCOPA® may increase the possibility of upper gastrointestinal hemorrhage in patients with a history of peptic ulcer.

Neuroleptic Malignant Syndrome (NMS)

Sporadic cases of a symptom complex resembling NMS have been reported in association with dose reductions or withdrawal of therapy with carbidopa-levodopa. Therefore, patients should be observed carefully when the dosage of PARCOPA® is reduced abruptly or discontinued, especially if the patient is receiving neuroleptics.

NMS is an uncommon but life-threatening syndrome characterized by fever or hyperthermia. Neurological findings, including muscle rigidity, involuntary movements, altered consciousness, mental status changes; other disturbances, such as autonomic dysfunction, tachycardia, tachypnea, sweating, hyper- or hypotension; laboratory findings, such as creatine phosphokinase elevation, leukocytosis, myoglobinuria, and increased serum myoglobin have been reported.

The early diagnosis of this condition is important for the appropriate management of these patients. Considering NMS as a possible diagnosis and ruling out other acute illnesses
(e.g., pneumonia, systemic infection, etc.) is essential. This may be especially complex if the clinical presentation includes both serious medical illness and untreated or inadequately treated extrapyramidal signs and symptoms (EPS). Other important considerations in the differential diagnosis include central anticholinergic toxicity, heat stroke, drug fever, and primary central nervous system (CNS) pathology.

The management of NMS should include: 1) intensive symptomatic treatment and medical monitoring and 2) treatment of any concomitant serious medical problems for which specific treatments are available. Dopamine agonists, such as bromocriptine, and muscle relaxants, such as dantrolene, are often used in the treatment of NMS, however, their effectiveness has not been demonstrated in controlled studies.

Precautions

General

As with levodopa, periodic evaluations of hepatic, hematopoietic, cardiovascular, and renal function are recommended during extended therapy.

Patients with chronic wide-angle glaucoma may be treated cautiously with PARCOPA® provided the intraocular pressure is well controlled and the patient is monitored carefully for changes in intraocular pressure during therapy.

Information for patients

Phenylketonurics

Phenylketonuric patients should be informed that PARCOPA® contains phenylalanine 3.4 mg per 25/100 orally disintegrating tablet, 3.4 mg per 10/100 orally disintegrating tablet, and 8.4 mg per 25/250 orally disintegrating tablet.

Patients should be instructed not to remove PARCOPA® Tablets from the bottle until just prior to dosing. With dry hands, the tablet should be gently removed and immediately placed on the tongue to dissolve and be swallowed with the saliva.

The patient should be informed that PARCOPA® is an immediate-release formulation of carbidopa-levodopa that is designed to begin release of ingredients within 30 minutes. It is important that PARCOPA® be taken at regular intervals according to the schedule outlined by the physician. The patient should be cautioned not to change the prescribed dosage regimen and not to add any additional antiparkinson medications, including other carbidopa-levodopa preparations, without first consulting the physician.

Patients should be advised that sometimes a “wearing-off” effect may occur at the end of the dosing interval. The physician should be notified if such response poses a problem to lifestyle.

Patients should be advised that occasionally, dark color (red, brown, or black) may appear in saliva, urine, or sweat after ingestion of PARCOPA®. Although the color appears to be clinically insignificant, garments may become discolored.

The patient should be advised that a change in diet to foods that are high in protein may delay the absorption of levodopa and may reduce the amount taken up in the circulation. Excessive acidity also delays stomach emptying, thus delaying the absorption of levodopa. Iron salts (such as in multi-vitamin tablets) may also reduce the amount of levodopa available to the body. The above factors may reduce the clinical effectiveness of the levodopa or carbidopa-levodopa therapy.

NOTE: The suggested advice to patients being treated with PARCOPA® is intended to aid in the safe and effective use of this medication. It is not a disclosure of all possible adverse or intended effects.

Laboratory tests

Abnormalities in laboratory tests may include elevations of liver function tests such as alkaline phosphatase, SGOT (AST), SGPT (ALT), lactic dehydrogenase, and bilirubin. Abnormalities in blood urea nitrogen and positive Coombs test have also been reported. Commonly, levels of blood urea nitrogen, creatinine, and uric acid are lower during administration of carbidopa-levodopa than with levodopa.

Carbidopa-levodopa may cause a false-positive reaction for urinary ketone bodies when a test tape is used for determination of ketonuria. This reaction will not be altered by boiling the urine specimen. False-negative tests may result with the use of glucose-oxidase methods of testing for glucosuria.

Cases of falsely diagnosed pheochromocytoma in patients on carbidopa-levodopa therapy have been reported very rarely. Caution should be exercised when interpreting the plasma and urine levels of catecholamines and their metabolites in patients on levodopa or carbidopa-levodopa therapy.

Interactions

Drug interactions

Caution should be exercised when the following drugs are administered concomitantly with PARCOPA® (carbidopa-levodopa orally disintegrating tablets).

Symptomatic postural hypotension has occurred when carbidopa-levodopa was added to the treatment of a patient receiving antihypertensive drugs. Therefore, when therapy with PARCOPA® is started, dosage adjustment of the antihypertensive drug may be required.

For patients receiving MAO inhibitors (Type A or B), see Contraindications. Concomitant therapy with selegiline and carbidopa-levodopa may be associated with severe orthostatic hypotension not attributable to carbidopa-levodopa alone (see Contraindications).

There have been rare reports of adverse reactions, including hypertension and dyskinesia, resulting from the concomitant use of tricyclic antidepressants and carbidopa-levodopa.

Dopamine D2 receptor antagonists (e.g., phenothiazines, butyrophenones, risperidone) and isoniazid may reduce the therapeutic effects of levodopa. In addition, the beneficial effects of levodopa in Parkinson’s disease have been reported to be reversed by phenytoin and papaverine. Patients taking these drugs with PARCOPA® should be carefully observed for loss of therapeutic response.

Iron salts may reduce the bioavailability of levodopa and carbidopa. The clinical relevance is unclear.

Although metoclopramide may increase the bioavailability of levodopa by increasing gastric emptying, metoclopramide may also adversely affect disease control by its dopamine receptor antagonistic properties.

Carcinogenesis, mutagenesis, impairment of fertility

In a two-year bioassay of carbidopa and levodopa, no evidence of carcinogenicity was found in rats receiving doses of approximately two times the maximum daily human dose of carbidopa and four times the maximum daily human dose of levodopa.

In reproduction studies with carbidopa and levodopa, no effects on fertility were found in rats receiving doses of approximately two times the maximum daily human dose of carbidopa and four times the maximum daily human dose of levodopa.

Pregnancy

Pregnancy Category C

No teratogenic effects were observed in a study in mice receiving up to 20 times the maximum recommended human dose of carbidopa and levodopa. There was a decrease in the number of live pups delivered by rats receiving approximately two times the maximum recommended human dose of carbidopa and approximately five times the maximum recommended human dose of levodopa during organogenesis. Carbidopa and levodopa caused both visceral and skeletal malformations in rabbits at all doses and ratios of carbidopa/levodopa tested, which ranged from 10 times/5 times the maximum recommended human dose of carbidopa/levodopa to 20 times/10 times the maximum recommended human dose of carbidopa/levodopa.

There are no adequate or well-controlled studies in pregnant women. It has been reported from individual cases that levodopa crosses the human placental barrier, enters the fetus, and is metabolized. Carbidopa concentrations in fetal tissue appeared to be minimal. Use of PARCOPA® in women of childbearing potential requires that the anticipated benefits of the drug be weighed against possible hazards to mother and child.

Nursing mothers

It is not known whether this drug is excreted in human milk. Because many drugs are excreted in human milk, caution should be exercised when PARCOPA® is administered to a nursing woman.

Pediatric use

Safety and effectiveness in pediatric patients have not been established. Use of the drug in patients below the age of 18 is not recommended.

Adverse Reactions

The most common adverse reactions reported with carbidopa-levodopa therapy have included dyskinesias, such as choreiform, dystonic, and other involuntary movements and nausea.

The following other adverse reactions have been reported with carbidopa-levodopa:

Body as a Whole: chest pain, asthenia.

Cardiovascular: cardiac irregularities, hypotension, orthostatic effects including orthostatic hypotension, hypertension, syncope, phlebitis, palpitation.

Gastrointestinal: dark saliva, gastrointestinal bleeding, development of duodenal ulcer, anorexia, vomiting, diarrhea, constipation, dyspepsia, dry mouth, taste alterations.

Hematologic: agranulocytosis, hemolytic and nonhemolytic anemia, thrombocytopenia, leukopenia.

Hypersensitivity: angioedema, urticaria, pruritus, Henoch-Schonlein purpura, bullous lesions (including pemphigus-like reactions).

Musculoskeletal: back pain, shoulder pain, muscle cramps.

Nervous System/Psychiatric: psychotic episodes including delusions, hallucinations, and paranoid ideation, neuroleptic malignant syndrome (see Warnings), bradykinetic episodes (“on-off” phenomenon), confusion, agitation, dizziness, somnolence, dream abnormalities including nightmares, insomnia, paresthesia, headache, depression with or without development of suicidal tendencies, dementia, increased libido. Convulsions also have occurred; however, a causal relationship with carbidopa-levodopa has not been established.

Respiratory: dyspnea, upper respiratory infection.

Skin: rash, increased sweating, alopecia, dark sweat.

Urogenital: urinary tract infection, urinary frequency, dark urine.

Laboratory Tests: decreased hemoglobin and hematocrit; abnormalities in alkaline phosphatase, SGOT (AST), SGPT (ALT), lactic dehydrogenase, bilirubin, blood urea nitrogen (BUN), Coombs test; elevated serum glucose; white blood cells, bacteria, and blood in the urine.

Other adverse reactions that have been reported with levodopa alone and with various carbidopa-levodopa formulations, and may occur with PARCOPA® are:

Body as a Whole: abdominal pain and distress, fatigue.

Cardiovascular: myocardial infarction.

Gastrointestinal: gastrointestinal pain, dysphagia, sialorrhea, flatulence, bruxism, burning sensation of the tongue, heartburn, hiccups.

Metabolic: edema, weight gain, weight loss.

Musculoskeletal: leg pain.

Nervous System/Psychiatric: ataxia, extrapyramidal disorder, falling, anxiety, gait abnormalities, nervousness, decreased mental acuity, memory impairment, disorientation, euphoria, blepharospasm (which may be taken as an early sign of excess dosage; consideration of dosage reduction may be made at this time), trismus, increased tremor, numbness, muscle twitching, activation of latent Horner’s syndrome, peripheral neuropathy.

Respiratory: pharyngeal pain, cough.

Skin: malignant melanoma (see also Contraindications), flushing.

Special Senses: oculogyric crises, diplopia, blurred vision, dilated pupils.

Urogenital: urinary retention, urinary incontinence, priapism.

Miscellaneous: bizarre breathing patterns, faintness, hoarseness, malaise, hot flashes, sense of stimulation.

Laboratory Tests: decreased white blood cell count and serum potassium; increased serum creatinine and uric acid; protein and glucose in urine.

Overdosage

Management of acute overdosage with PARCOPA® is the same as management of acute overdosage with levodopa. Pyridoxine is not effective in reversing the actions of PARCOPA®.

General supportive measures should be employed, along with immediate gastric lavage. Intravenous fluids should be administered judiciously and an adequate airway maintained. Electrocardiographic monitoring should be instituted and the patient carefully observed for the development of arrhythmias; if required, appropriate anti-arrhythmic therapy should be given. The possibility that the patient may have taken other drugs as well as PARCOPA® should be taken into consideration. To date, no experience has been reported with dialysis; hence, its value in overdosage is not known.

Based on studies in which high doses of levodopa and/or carbidopa were administered, a significant proportion of rats and mice given single oral doses of levodopa of approximately 1500-2000 mg/kg are expected to die. A significant proportion of infant rats of both sexes are expected to die at a dose of 800 mg/kg. A significant proportion of rats are expected to die after treatment with similar doses of carbidopa. The addition of carbidopa in a 1:10 ratio with levodopa increases the dose at which a significant proportion of mice are expected to die to
3360 mg/kg.

Dosage and Administration

Instructions for Use/Handling PARCOPA® Tablets

Just prior to administration, GENTLY remove the tablet from the bottle with dry hands. IMMEDIATELY place the PARCOPA® Tablet on top of the tongue where it will dissolve in seconds, then swallow with saliva. Administration with liquid is not necessary.

The optimum daily dosage of PARCOPA® must be determined by careful titration in each patient. PARCOPA® is available in a 1:4 ratio of carbidopa to levodopa (PARCOPA® 25/100) as well as 1:10 ratio (PARCOPA® 25/250 and PARCOPA® 10/100). Tablets of the two ratios may be given separately or combined as needed to provide the optimum dosage.

Studies show that peripheral dopa decarboxylase is saturated by carbidopa at approximately 70 to 100 mg a day. Patients receiving less than this amount of carbidopa are more likely to experience nausea and vomiting.

Usual Initial Dosage

Dosage is best initiated with one tablet of PARCOPA® 25/100 three times a day. This dosage schedule provides 75 mg of carbidopa per day. Dosage may be increased by one tablet every day or every other day, as necessary, until a dosage of eight tablets of PARCOPA® 25/100 a day is reached.

If PARCOPA® 10/100 is used, dosage may be initiated with one tablet three or four times a day. However, this will not provide an adequate amount of carbidopa for many patients. Dosage may be increased by one tablet every day or every other day until a total of eight tablets (2 tablets q.i.d.) is reached.

How to Transfer Patients from Levodopa

Levodopa must be discontinued at least twelve hours before starting PARCOPA® (carbidopa-levodopa orally disintegrating tablets). A daily dosage of PARCOPA® should be chosen that will provide approximately 25 percent of the previous levodopa dosage. Patients who are taking less than 1500 mg of levodopa a day should be started on one tablet of PARCOPA® 25/100 three or four times a day. The suggested starting dosage for most patients taking more than 1500 mg of levodopa is one tablet of PARCOPA® 25/250 three or four times a day.

Maintenance

Therapy should be individualized and adjusted according to the desired therapeutic response. At least 70 to 100 mg of carbidopa per day should be provided. When a greater proportion of carbidopa is required, one tablet of PARCOPA® 25/100 may be substituted for each tablet of PARCOPA® 10/100. When more levodopa is required, PARCOPA® 25/250 should be substituted for PARCOPA® 25/100 or PARCOPA® 10/100. If necessary, the dosage of PARCOPA® 25/250 may be increased by one-half or one tablet every day or every other day to a maximum of eight tablets a day. Experience with total daily dosages of carbidopa greater than 200 mg is limited.

Because both therapeutic and adverse responses occur more rapidly with PARCOPA® than with levodopa alone, patients should be monitored closely during the dose adjustment period. Specifically, involuntary movements will occur more rapidly with PARCOPA® than with levodopa. The occurrence of involuntary movements may require dosage reduction. Blepharospasm may be a useful early sign of excess dosage in some patients.

Addition of Other Antiparkinsonian Medications

Standard drugs for Parkinson’s disease, other than levodopa without a decarboxylase inhibitor, may be used concomitantly while PARCOPA® is being administered, although dosage adjustments may be required.

Interruption of Therapy

Sporadic cases of a symptom complex resembling Neuroleptic Malignant Syndrome (NMS) have been associated with dose reductions and withdrawal of carbidopa-levodopa. Patients should be observed carefully if abrupt reduction or discontinuation of PARCOPA® is required, especially if the patient is receiving neuroleptics. (See Warnings.)

If general anesthesia is required, PARCOPA® may be continued as long as the patient is permitted to take fluids and medication by mouth. If therapy is interrupted temporarily, the patient should be observed for symptoms resembling NMS, and the usual daily dosage may be administered as soon as the patient is able to take oral medication.

How Supplied

PARCOPA® (carbidopa-levodopa orally disintegrating tablets) 25/100 are yellow, round, flat-faced, mint-flavored, scored and engraved “25/100” on the unscored side and “SP” above and “342” below the score on the other side. They are supplied as follows:

Bottles of 100NDC 0091-3342-01

PARCOPA® (carbidopa-levodopa orally disintegrating tablets) 10/100 are blue, round, flat-faced, mint-flavored, scored and engraved “10/100” on the unscored side and “SP” above and “341” below the score on the other side. They are supplied as follows:

Bottles of 100NDC 0091-3341-01

PARCOPA® (carbidopa-levodopa orally disintegrating tablets) 25/250 are blue, round, flat-faced, mint-flavored, scored, and engraved “25/250” on the unscored side and “SP” above and “343” below the score on the other side. They are supplied as follows:

Bottles of 100NDC 0091-3343-01

Storage

Store at 20° to 25°C (68° to 77°F); excursions permitted between 15° to 30°C (59° to 86°F) [See USP Controlled Room Temperature]. Protect from moisture and light.

Dispense in a tight, light-resistant container as defined in the USP/NF.

By:
CIMA LABS INC.® Eden Prairie, MN 55344, USA